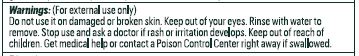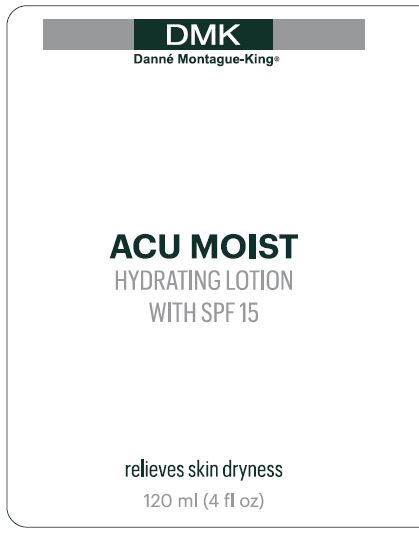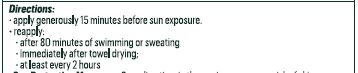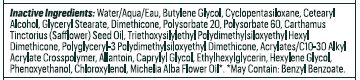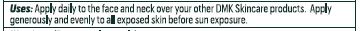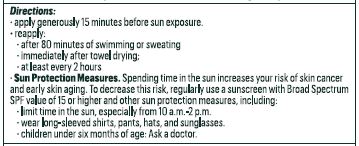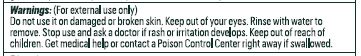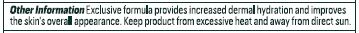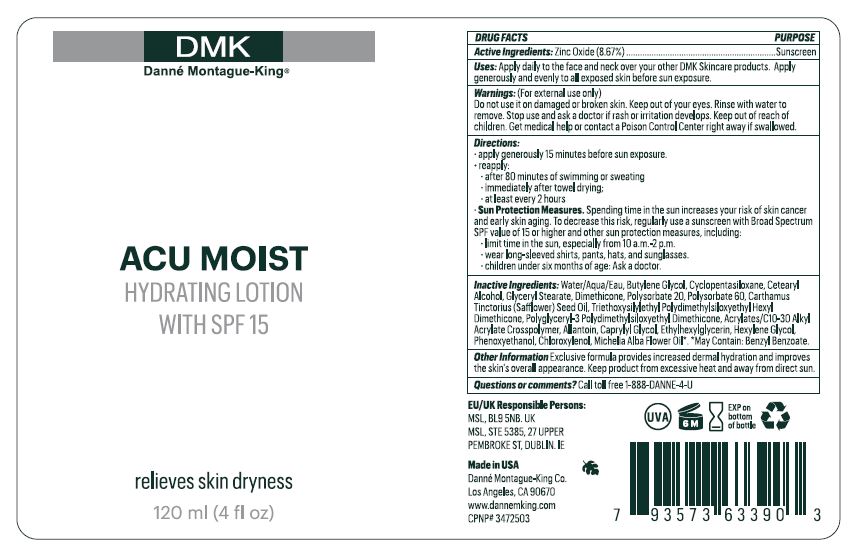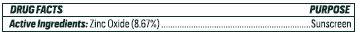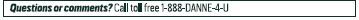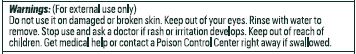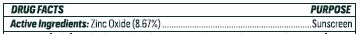 DRUG LABEL: Acu Moist
NDC: 81537-103 | Form: LOTION
Manufacturer: Danne Montague King
Category: otc | Type: HUMAN OTC DRUG LABEL
Date: 20240719

ACTIVE INGREDIENTS: ZINC OXIDE 8.67 g/100 mL
INACTIVE INGREDIENTS: MAGNOLIA CHAMPACA FLOWER OIL 0.15 g/100 mL; CYCLOMETHICONE 5 5.09 g/100 mL; POLYSORBATE 60 1.75 g/100 mL; ACRYLATES/C10-30 ALKYL ACRYLATE CROSSPOLYMER (60000 MPA.S) 0.5 g/100 mL; PHENOXYETHANOL 0.63 g/100 mL; POLYSORBATE 20 2.5 g/100 mL; WATER 61.68 g/100 mL; BUTYLENE GLYCOL 5.25 g/100 mL; DIMETHICONE 2.5 g/100 mL; SAFFLOWER OIL 1.75 g/100 mL; TRIETHOXYSILYLETHYL POLYDIMETHYLSILOXYETHYL HEXYL DIMETHICONE 0.83 g/100 mL; POLYGLYCERYL-3 POLYDIMETHYLSILOXYETHYL DIMETHICONE (4000 MPA.S) 0.83 g/100 mL; ALLANTOIN 0.5 g/100 mL; CAPRYLYL GLYCOL 0.31 g/100 mL; ETHYLHEXYLGLYCERIN 0.19 g/100 mL; HEXYLENE GLYCOL 0.13 g/100 mL; CHLOROXYLENOL 0.25 g/100 mL

Acu Moist SPF 15